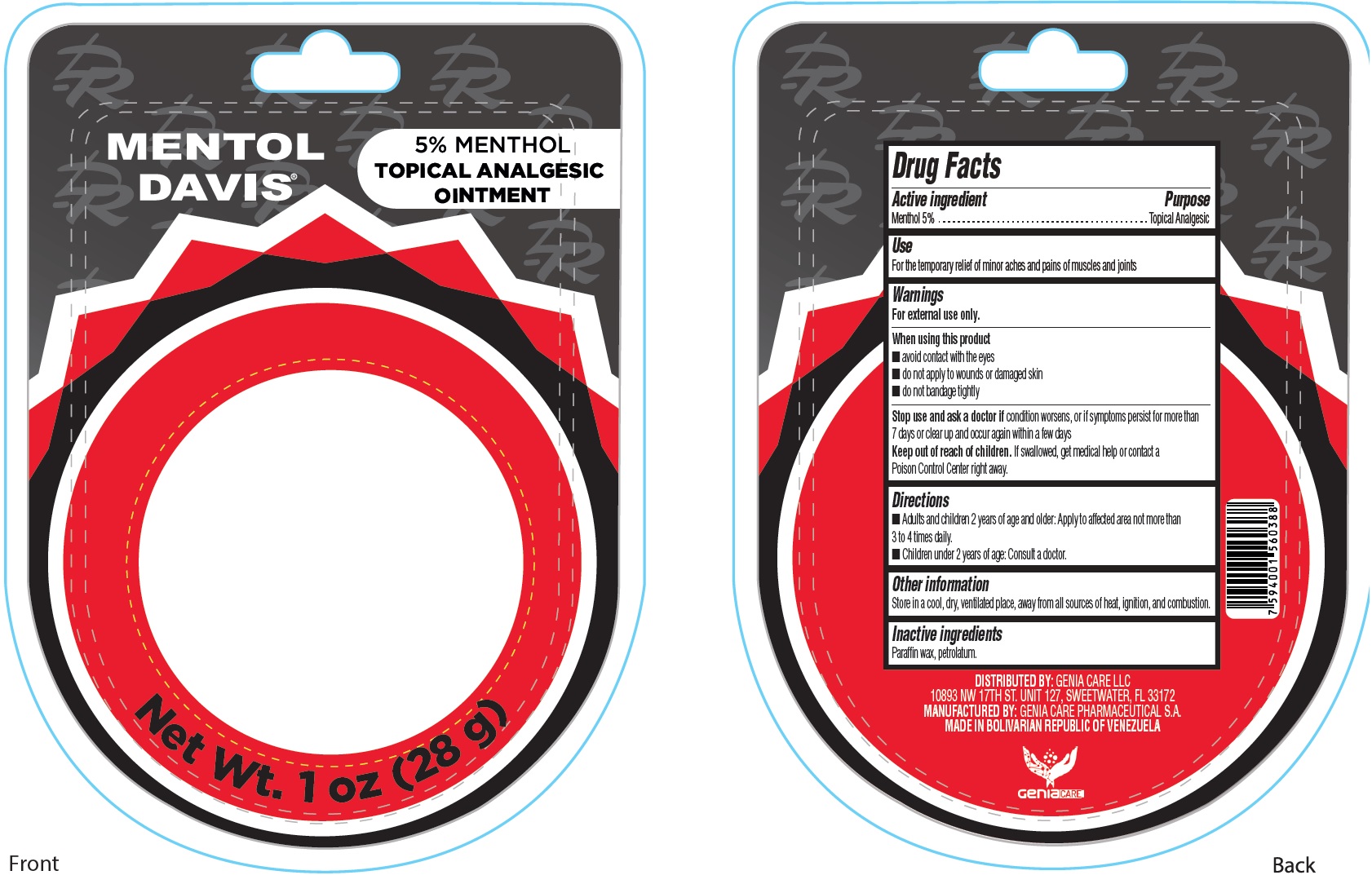 DRUG LABEL: Menthol Davis Analgesic
NDC: 82480-000 | Form: OINTMENT
Manufacturer: Genia Care Phamaceutical S.A.
Category: otc | Type: HUMAN OTC DRUG LABEL
Date: 20220613

ACTIVE INGREDIENTS: MENTHOL 50 mg/1 g
INACTIVE INGREDIENTS: PARAFFIN; PETROLATUM

Menthol Davis Topical Analgesic Ointment

Active ingredient

Menthol 5%

Purpose

Topical Analgesic

Use

For the temporary relief of minor aches and pains of muscles and joints

Warnings

For external use only.

When using this product

- avoid contact with the eyes
- do not apply to wounds or damaged skin
- do not bandage tightly

Stop use and ask a doctor if

condition worsens, or if symptoms persist for more than 7 days or clear up and occur again within a few days

Keep out of reach of children.

If swallowed, get medical help or contact a Poison Control Center right away.

Directions

- Adults and children 2 years of age and older: Apply to affected area not more than 3 to 4 times daily.
- Children under 2 years of age: Consult a doctor.

Other information

Store in a cool, dry, ventilated place, away from all sources of heat, ignition, and combustion.

Inactive ingredients

Paraffin wax, petrolatum.